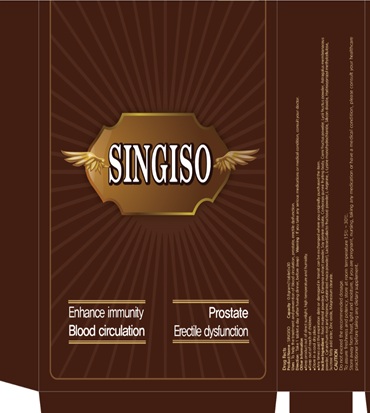 DRUG LABEL: SINGISO 101 (0.8g)
NDC: 69720-3001 | Form: TABLET
Manufacturer: Sae In Dang Co., Ltd.
Category: otc | Type: HUMAN OTC DRUG LABEL
Date: 20160902

ACTIVE INGREDIENTS: ASIAN GINSENG 17.19 g/100 g
INACTIVE INGREDIENTS: PUMPKIN SEED; CORDYCEPS GUNNII FRUITING BODY; MAGNESIUM STEARATE; LEPIDIUM MEYENII ROOT; SOY PROTEIN; BOMBYX MORI LARVA; CORNUS OFFICINALIS FRUIT; FU LING; LACTOSE; LYSINE HYDROCHLORIDE; SILICON DIOXIDE; 1-OCTACOSANOL; SUCROSE; ZINC OXIDE; HYPROMELLOSE 2208 (4000 MPA.S); SERENOA REPENS WHOLE; GINGER; LYCIUM BARBARUM FRUIT; ARGININE; TURNERA DIFFUSA LEAFY TWIG

ACTIVE INGREDIENTS

Red ginseng 17.19%

PURPOSE

Stimulant

KEEP OUT OF REACH OF CHILDREN

USES

to help the treatment and prevention of blood circulation, antioxidant effect, memory improvement, prostate, erectile dysfunction

WARNING

If you take any serious medications or medical condition, consult your doctor.

DIRECTION

Take 1 tablet a day (after having dinner, before sleep)

INACTIVE INGREDIENT

Food material powders [ERC-101] (total 62.5%)
- Damiana extract powder 20%
- Maca(Lepidium meyenii) extract powder 10%
- Pumpkin seed extract powder 10%
- Soy protein isolate 10%
- Ginger(Zingiber afficinale Roscoe) powder 10%
- Cordyceps militaris powder 10%
- Lycii fructus powder 10%
- Silkworm(Bombyx mori L.) powder 10%
- Corni fructus powder 5%
- Poria cocos powder 3%
- Octacosanol powder 2%
Lactose (Galacto fructose) powder 12.0%
L-Arginine 3.9%
Silicon dioxide 1.8%
Magnesium stearate 1.08%
L-Lysine Monohydrochloride 0.78%
Zinc oxide 0.15%
Hydroxypropyl methylcellulose 0.54%
Sucrose fatty acid ester 0.03%
Saw Palmetto(Serenoa repens) extract 0.03%

OTHER INFORMATION

- Keep product out of direct sunlight, high temperature and humidity.
- Store in a cool dry place.
- Any items past the expiration date or damaged in transit can be exchanged where you originally purchased the item

SPL UNCLASSIFIED SECTION

Do not exceed the recommended dosage.

To assure freshness and potency, store at room temperature 15oC - 30oC.

Store away from heat, light and moisture, if you are pregnant, nursing, taking any medication or have a medical condition, please consult your healthcare practitioner before taking any dietary supplement.